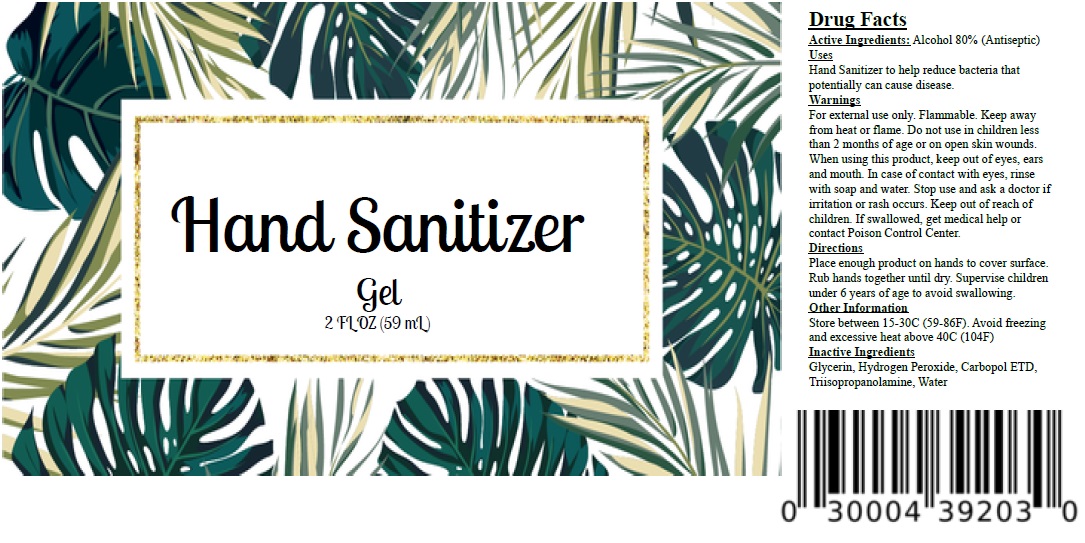 DRUG LABEL: Zing Hand Sanitizer
NDC: 74953-415 | Form: GEL
Manufacturer: Zing Brothers LLC
Category: otc | Type: HUMAN OTC DRUG LABEL
Date: 20200415

ACTIVE INGREDIENTS: ALCOHOL 80 mL/100 mL
INACTIVE INGREDIENTS: GLYCERIN; HYDROGEN PEROXIDE; CARBOMER INTERPOLYMER TYPE B (ALLYL PENTAERYTHRITOL CROSSLINKED); TRIISOPROPANOLAMINE; WATER

Zing Hand Sanitizer Gel

Active Ingredients:

Alcohol 80%

Purpose

(Antiseptic)

Uses

Hand Sanitizer to help reduce bacteria that potentially can cause disease.

Warnings

For external use only. Flammable. Keep away from heat or flame. Do not use in children less than 2 months of age or on open skin wounds. When using this product, keep out of eyes, ears and mouth. In case of contact with eyes, rinse with soap and water. Stop use and ask a doctor if irritation or rash occurs.

Keep out of reach of children. If swallowed, get medical help or contact Poison Control Center.

Directions

Place enough product on hands to cover surface. Rub hands together until dry. Supervise children under 6 years of age to avoid swallowing.

Other Information

Store between 15-30C (59-86F). Avoid freezing and excessive heat above 40C (104F)

Inactive Ingredients

Glycerin, Hydrogen Peroxide, Carbopol ETD, Triisopropanolamine, Water